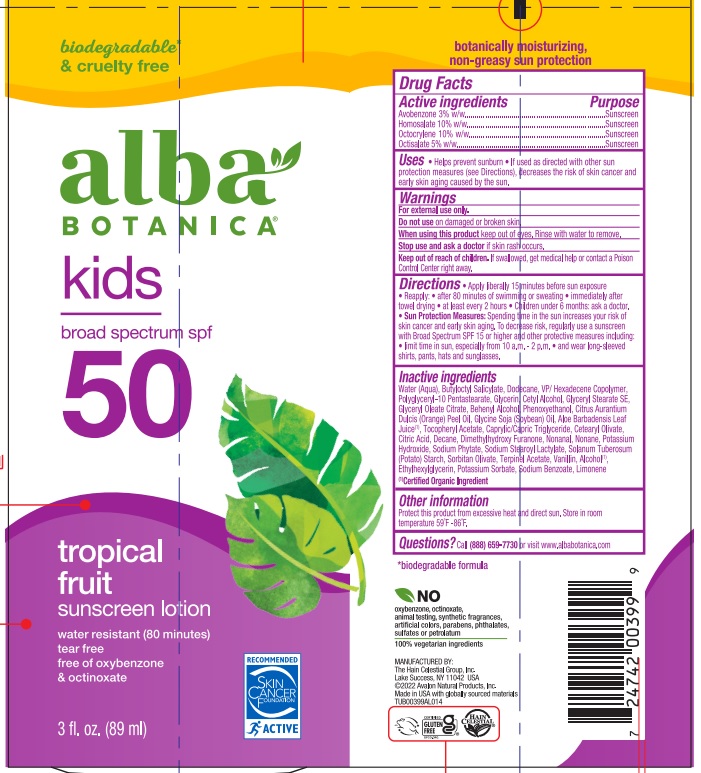 DRUG LABEL: Alba Botanica SPF 50 Sunscreen
NDC: 61995-2029 | Form: LOTION
Manufacturer: The Hain Celestial Group, Inc
Category: otc | Type: HUMAN OTC DRUG LABEL
Date: 20241128

ACTIVE INGREDIENTS: AVOBENZONE 3 g/100 g; OCTOCRYLENE 10 g/100 g; OCTISALATE 5 g/100 g; HOMOSALATE 10 g/100 g
INACTIVE INGREDIENTS: VANILLIN; LIMONENE, (+)-; PHENOXYETHANOL; BUTYLOCTYL SALICYLATE; POLYGLYCERYL-10 PENTASTEARATE; CAPRYLIC/CAPRIC TRIGLYCERIDE; SORBITAN OLIVATE; ALCOHOL; CETEARYL OLIVATE; ANHYDROUS CITRIC ACID; SODIUM BENZOATE; ALOE VERA WHOLE; BENZYL ALCOHOL; WATER; GLYCERYL STEARATE SE; POTASSIUM SORBATE; VINYLPYRROLIDONE/HEXADECENE COPOLYMER; CETYL ALCOHOL; GLYCERIN; .ALPHA.-TOCOPHEROL ACETATE; NONANAL; ETHYLHEXYLGLYCERIN; SOYBEAN OIL; GLYCERYL OLEATE; BEHENYL BEHENATE; SODIUM STEAROYL LACTYLATE; POTASSIUM HYDROXIDE; ORANGE PEEL; .ALPHA.-TERPINYL ACETATE, (+)-; DIMETHYLHYDROXY FURANONE; STARCH, POTATO; C9-11 ALKANE/CYCLOALKANE; HEXASODIUM PHYTATE

Alba SPF 50 Sunscreen Lotion

ACTIVE INGREDIENT

Avobenzone 3%

Homosalate 10%

Octocrylene 10%

Octisalate 5%

DOSAGE AND ADMINISTRATION

● Apply liberally 15 minutes before sun exposure ● Reapply: ● after 80 minutes of swimming or sweating ● immediately after towel drying ● at least every 2 hours ● Children under 6 months of age: ask a doctor

● Sun Protection Measures: Spending time in the sun increases your risk of skin cancer and early skin aging. To decrease this risk, regularly use sunscreen with a Broad Spectrum SPF value of 15 or higher and other sun protection measures including:

● limit time in the sun, especially from 10 am - 2 pm

● wear long-sleeved shirts, pants, hats, and sunglasses

PURPOSE

Sunscreen

WARNINGS

For external use only. Do not use on broken or damaged skin. When using this product, keep out of eyes. Rinse with water to remove. Stop use and ask a doctor if skin rash occurs. If swallowed, get medical help or contact a Poison Control Center right away.

Keep out of reach of children.

INACTIVE INGREDIENT

Water (Aqua), Butyloctyl Salicylate, Dodecane, VP/Hexadecene Copolymer, Polyglyceryl-10 Pentastearate, Glycerin, Cetyl Alcohol, Glyceryl Stearate SE, Glyceryl Oleate Citrate, Behenyl Alcohol, Phenoxyethanol, Citrus Aurantium Dulcis (Orange) Peel Oil, Glycine Soja (Soybean) Oil, Aloe Barbadensis Leaf Juice (1), Tocopheryl Acetate, Caprylic/Capric Triglyceride, Cetearyl Olivate, Citric Acid, Decane, Dimethylhydroxy Furanone, Nonanal, Nonane, Potassium Hydroxide, Sodium Phytate, Sodium Stearoyl Lactylate, Solanum Tuberosum (Potato) Starch, Sorbitan Olivate, Terpinel Acetate, Vanillin, Alcohol (1), Ethylhexylglycerin, Potassium Sorbate, Sodium Benzoate, Limonene

(1) Certified Organic Ingredient

INDICATIONS AND USAGE

- Helps prevent sunburn
- If used as directed with other sun protection measures (see Directions), decreases the risk of skin cancer and early skin aging caused by the sun